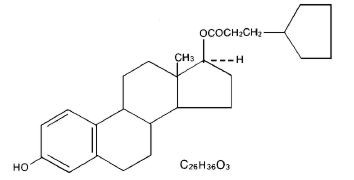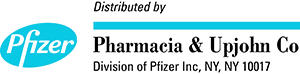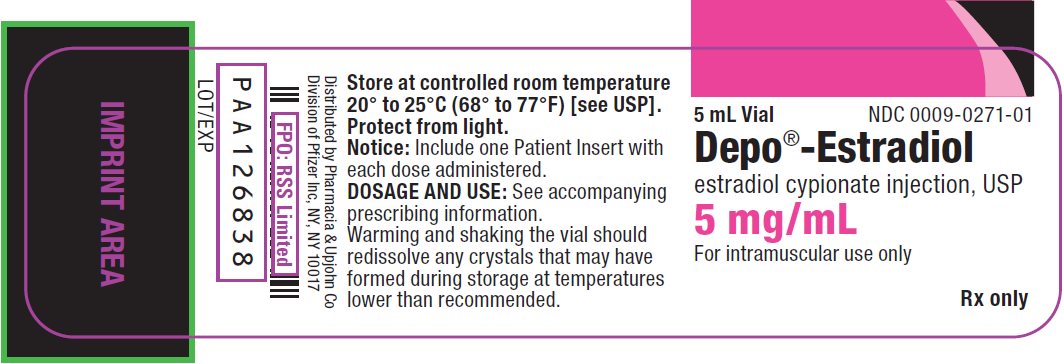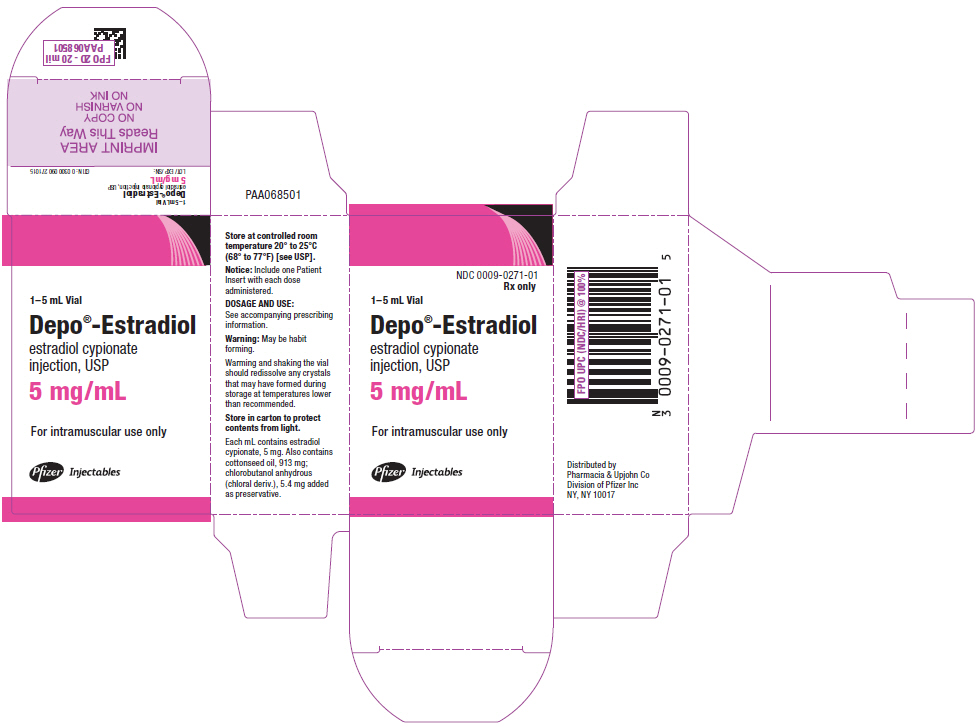 DRUG LABEL: Depo-Estradiol
NDC: 0009-0271 | Form: INJECTION
Manufacturer: Pharmacia & Upjohn Company LLC
Category: prescription | Type: HUMAN PRESCRIPTION DRUG LABEL
Date: 20240228

ACTIVE INGREDIENTS: ESTRADIOL CYPIONATE 5 mg/1 mL
INACTIVE INGREDIENTS: COTTONSEED OIL 913 mg/1 mL; CHLOROBUTANOL 5.4 mg/1 mL

DEPO®-ESTRADIOL
Estradiol cypionate injection, USP

WARNINGS

ESTROGENS INCREASE THE RISK OF ENDOMETRIAL CANCER

Close clinical surveillance of all women taking estrogens is important. Adequate diagnostic measures including endometrial sampling, when indicated, should be undertaken to rule out malignancy in all cases of undiagnosed persistent or recurring abnormal vaginal bleeding. There is currently no evidence that the use of "natural" estrogens results in a different endometrial risk profile than "synthetic" estrogens at equivalent estrogen doses. (See WARNINGS, malignant neoplasms, Endometrial cancer.)

CARDIOVASCULAR AND OTHER RISKS

Estrogens with and without progestins should not be used for the prevention of cardiovascular disease. (See WARNINGS, Cardiovascular disorders.)

The Women's Health Initiative (WHI) study reported increased risks of myocardial infarction, stroke, invasive breast cancer, pulmonary emboli, and deep vein thrombosis in postmenopausal women (50 to 79 years of age) during 5 years of treatment with oral conjugated estrogens (CE 0.625 mg) combined with medroxyprogesterone acetate (MPA 2.5 mg) relative to placebo. (See CLINICAL PHARMACOLOGY, Clinical Studies.)

The Women's Health Initiative Memory Study (WHIMS), a substudy of WHI, reported increased risk of developing probable dementia in postmenopausal women 65 years of age or older during 4 years of treatment with oral conjugated estrogens plus medroxyprogesterone acetate relative to placebo. It is unknown whether this finding applies to younger postmenopausal women or to women taking estrogen-alone therapy. (See CLINICAL PHARMACOLOGY, Clinical Studies.)

Other doses of conjugated estrogens with medroxyprogesterone acetate, and other combinations and dosage forms of estrogens and progestins were not studied in the WHI clinical trials and, in the absence of comparable data, these risks should be assumed to be similar. Because of these risks, estrogens with or without progestins should be prescribed at the lowest effective doses and for the shortest duration consistent with treatment goals and risks for the individual woman.

DESCRIPTION

DEPO-Estradiol Injection contains estradiol cypionate for intramuscular use. Each mL contains:

5 mg/mL—5 mg estradiol cypionate, 5.4 mg chlorobutanol anhydrous (chloral derivative) added as preservative; in 913 mg cottonseed oil.

Warning: Chlorobutanol may be habit forming. The structural formula is represented below:

DEPO-Estradiol contains an oil soluble ester of estradiol 17β. The chemical name for estradiol cypionate is estradiol 17-cyclopentanepropionate.

CLINICAL PHARMACOLOGY

Endogenous estrogens are largely responsible for the development and maintenance of the female reproductive system and secondary sexual characteristics. Although circulating estrogens exist in a dynamic equilibrium of metabolic interconversions, estradiol is the principal intracellular human estrogen and is substantially more potent than its metabolites, estrone and estriol, at the receptor level.

The primary source of estrogen in normally cycling adult women is the ovarian follicle, which secretes 70 to 500 mcg of estradiol daily, depending on the phase of the menstrual cycle. After menopause, most endogenous estrogen is produced by conversion of androstenedione, secreted by the adrenal cortex, to estrone by peripheral tissues. Thus, estrone and the sulfate conjugated form, estrone sulfate, are the most abundant circulating estrogens in postmenopausal women.

Estrogens act through binding to nuclear receptors in estrogen-responsive tissues. To date, two estrogen receptors have been identified. These vary in proportion from tissue to tissue.

Circulating estrogens modulate the pituitary secretion of the gonadotropins, luteinizing hormone (LH) and follicle stimulating hormone (FSH), through a negative feedback mechanism. Estrogens act to reduce the elevated levels of these hormones seen in postmenopausal women.

Absorption

When conjugated with aryl and alkyl groups for parenteral administration, the rate of absorption of oily preparations is slowed with a prolonged duration of action, such that a single intramuscular injection of estradiol valerate or estradiol cypionate is absorbed over several weeks.

Distribution

The distribution of exogenous estrogens is similar to that of endogenous estrogens. Estrogens are widely distributed in the body and are generally found in higher concentrations in the sex hormone target organs. Estrogens circulate in the blood largely bound to sex hormone binding globulin (SHBG) and albumin.

Metabolism

Exogenous estrogens are metabolized in the same manner as endogenous estrogens. Circulating estrogens exist in a dynamic equilibrium of metabolic interconversions. These transformations take place mainly in the liver. Estradiol is converted reversibly to estrone, and both can be converted to estriol, which is the major urinary metabolite. Estrogens also undergo enterohepatic recirculation via sulfate and glucuronide conjugation in the liver, biliary secretion of conjugates into the intestine, and hydrolysis in the gut followed by reabsorption. In postmenopausal women, a significant proportion of the circulating estrogens exist as sulfate conjugates, especially estrone sulfate, which serves as a circulating reservoir for the formation of more active estrogens.

Excretion

Estradiol, estrone, and estriol are excreted in the urine along with glucuronide and sulfate conjugates.

Drug Interactions

In vitro and in vivo studies have shown that estrogens are metabolized partially by cytochrome P450 3A4 (CYP3A4). Therefore, inducers or inhibitors of CYP3A4 may affect estrogen drug metabolism. Inducers of CYP3A4 such as St. John's Wort preparations (Hypericum perforatum), phenobarbital, carbamazepine, and rifampin may reduce plasma concentrations of estrogens, possibly resulting in a decrease in therapeutic effects and/or changes in the uterine bleeding profile. Inhibitors of CYP3A4 such as erythromycin, clarithromycin, ketoconazole, itraconazole, ritonavir and grapefruit juice may increase plasma concentrations of estrogens and may result in side effects.

Estrogen drug products administered by non oral routes are not subject to first-pass metabolism, but also undergo significant hepatic uptake, metabolism, and enterohepatic recycling.

Clinical Studies

Women's Health Initiative Studies

The Women's Health Initiative (WHI) enrolled a total of 27,000 predominantly healthy postmenopausal women to assess the risks and benefits of either the use of 0.625 mg conjugated estrogens (CE) per day alone or the use of oral 0.625 mg conjugated estrogens plus 2.5 mg medroxyprogesterone acetate (MPA) per day compared to placebo in the prevention of certain chronic diseases. The primary endpoint was the incidence of coronary heart disease (CHD) (nonfatal myocardial infarction and CHD death), with invasive breast cancer as the primary adverse outcome studied. A "global index" included the earliest occurrence of CHD, invasive breast cancer, stroke, pulmonary embolism (PE), endometrial cancer, colorectal cancer, hip fracture, or death due to other cause. The study did not evaluate the effects of CE or CE/MPA on menopausal symptoms.

The CE/MPA substudy was stopped early because, according to the predefined stopping rule, the increased risk of breast cancer and cardiovascular events exceeded the specified benefits included in the "global index." Results of the CE/MPA substudy, which included 16,608 women (average age of 63 years, range 50 to 79; 83.9% White, 6.5% Black, 5.5% Hispanic), after an average follow-up of 5.2 years are presented in Table 1 below:

Table 1: RELATIVE AND ABSOLUTE RISK SEEN IN THE CE/MPA SUBSTUDY OF WHI [adapted from JAMA, 2002; 288:321–333]
Event [a subset of the events was combined in a "global index," defined as the earliest occurrence of CHD events, invasive breast cancer, stroke, pulmonary embolism, endometrial cancer, colorectal cancer, hip fracture, or death due to other causes] | Relative Risk CE/MPA vs placebo at 5.2 Years (95% CI [nominal confidence intervals unadjusted for multiple looks and multiple comparisons]) | Placebo n = 8102 | CE/MPA n = 8506
Event [a subset of the events was combined in a "global index," defined as the earliest occurrence of CHD events, invasive breast cancer, stroke, pulmonary embolism, endometrial cancer, colorectal cancer, hip fracture, or death due to other causes] | Relative Risk CE/MPA vs placebo at 5.2 Years (95% CI [nominal confidence intervals unadjusted for multiple looks and multiple comparisons]) | Absolute Risk per 10,000 Person-years
CHD events | 1.29 (1.02–1.63) | 30 | 37
Non-fatal MI | 1.32 (1.02–1.72) | 23 | 30
CHD death | 1.18 (0.70–1.97) | 6 | 7
Invasive breast cancer [includes metastatic and non-metastatic breast cancer with the exception of in situ breast cancer] | 1.26 (1.00–1.59) | 30 | 38
Stroke | 1.41 (1.07–1.85) | 21 | 29
Pulmonary embolism | 2.13 (1.39–3.25) | 8 | 16
Colorectal cancer | 0.63 (0.43–0.92) | 16 | 10
Endometrial cancer | 0.83 (0.47–1.47) | 6 | 5
Hip fracture | 0.66 (0.45–0.98) | 15 | 10
Death due to causes other than the events above | 0.92 (0.74–1.14) | 40 | 37
Global index | 1.15 (1.03–1.28) | 151 | 170
Deep vein thrombosis [not included in Global Index] | 2.07 (1.49–2.87) | 13 | 26
Vertebral fractures | 0.66 (0.44–0.98) | 15 | 9
Other osteoporotic fractures | 0.77 (0.69–0.86) | 170 | 131

For those outcomes included in the "global index," the absolute excess risks per 10,000 person-years in the group treated with CE/MPA were 7 more CHD events, 8 more strokes, 8 more PEs, and 8 more invasive breast cancers, while absolute risk reductions per 10,000 person-years were 6 fewer colorectal cancers and 5 fewer hip fractures. The absolute excess risk of events included in the "global index" was 19 per 10,000 women-years. There was no difference between the groups in terms of all-cause mortality. (See BOXED WARNINGS, WARNINGS and PRECAUTIONS.)

Women's Health Initiative Memory Study

The Women's Health Initiative Memory Study (WHIMS), a substudy of WHI, enrolled 4,532 predominantly healthy postmenopausal women 65 years of age and older (47% were age 65 to 69 years, 35% were 70 to 74 years, and 18% were 75 years of age and older) to evaluate the effects of CE/MPA (0.625 mg conjugated estrogens plus 2.5 mg medroxyprogesterone acetate) on the incidence of probable dementia (primary outcome) compared with placebo.

After an average follow-up of 4 years, 40 women in the estrogen/progestin group (45 per 10,000 women-years) and 21 in the placebo group (22 per 10,000 women-years) were diagnosed with probable dementia. The relative risk of probable dementia in the hormone therapy group was 2.05 (95% CI, 1.21 to 3.48) compared to placebo. Differences between groups became apparent in the first year of treatment. It is unknown whether these findings apply to younger postmenopausal women. (See BOXED WARNINGS and WARNINGS, Dementia.)

Comparative clinical studies have demonstrated that estradiol cypionate produces estrogenic effects that are qualitatively the same as those produced by other estradiol esters. In menopausal women, the average duration of estrogenic effect (as measured by vaginal smear) following a single injection of 5 mg of estradiol cypionate was found to be approximately 3 to 4 weeks. Relief of vasomotor symptoms was observed to occur within 1 to 5 days and to be maintained for 1 to 8 weeks, with an average of approximately 5 weeks.

INDICATIONS AND USAGE

DEPO-Estradiol Injection is indicated in the treatment of:

1. Moderate to severe vasomotor symptoms associated with the menopause.
2. Hypoestrogenism due to hypogonadism.

CONTRAINDICATIONS

Estrogens should not be used in individuals with any of the following conditions:

1. Undiagnosed abnormal genital bleeding.
2. Known or suspected cancer of the breast.
3. Known or suspected estrogen-dependent neoplasia.
4. Active deep vein thrombosis, pulmonary embolism or history of these conditions.
5. Active or recent (e.g., within the past year) arterial thromboembolic disease (e.g., stroke, myocardial infarction).
6. Liver dysfunction or disease.
7. DEPO-Estradiol should not be used in patients with known hypersensitivity to its ingredients.
8. Known or suspected pregnancy. There is no indication for DEPO-Estradiol in pregnancy.

There appears to be little or no increased risk of birth defects in children born to women who have used estrogens and progestins from oral contraceptives inadvertently during early pregnancy. (See PRECAUTIONS.)

WARNINGS

See BOXED WARNINGS

1. Cardiovascular disorders

Estrogen and estrogen/progestin therapy have been associated with an increased risk of cardiovascular events such as myocardial infarction and stroke, as well as venous thrombosis and pulmonary embolism (venous thromboembolism or VTE). Should any of these occur or be suspected, estrogens should be discontinued immediately.

Risk factors for arterial vascular disease (e.g., hypertension, diabetes mellitus, tobacco use, hypercholesterolemia, and obesity) and/or venous thromboembolism (e.g., personal history or family history of VTE, obesity, and systemic lupus erythematosus) should be managed appropriately.

a. Coronary heart disease and stroke

In the Women's Health Initiative (WHI) study, an increase in the number of myocardial infarctions and strokes has been observed in women receiving CE compared to placebo. These observations are preliminary, and the study is continuing. (See CLINICAL PHARMACOLOGY, Clinical Studies.)

In the CE/MPA substudy of WHI, an increased risk of coronary heart disease (CHD) events (defined as nonfatal myocardial infarction and CHD death) was observed in women receiving CE/MPA compared to women receiving placebo (37 vs. 30 per 10,000 women-years). The increase in risk was observed in year one and persisted.

In the same substudy of WHI, an increased risk of stroke was observed in women receiving CE/MPA compared to women receiving placebo (29 vs. 21 per 10,000 women-years). The increase in risk was observed after the first year and persisted.

In postmenopausal women with documented heart disease (n = 2,763, average age 66.7 years) a controlled clinical trial of secondary prevention of cardiovascular disease (Heart and Estrogen/Progestin Replacement Study; HERS) treatment with CE/MPA (0.625 mg/2.5 mg per day) demonstrated no cardiovascular benefit. During an average follow-up of 4.1 years, treatment with CE/MPA did not reduce the overall rate of CHD events in postmenopausal women with established coronary heart disease. There were more CHD events in the CE/MPA-treated group than in the placebo group in year 1, but not during the subsequent years. Two thousand three hundred and twenty one women from the original HERS trial agreed to participate in an open-label extension of HERS, HERS II. Average follow-up in HERS II was an additional 2.7 years, for a total of 6.8 years overall. Rates of CHD events were comparable among women in the CE/MPA group and the placebo group in HERS, HERS II, and overall.

Large doses of estrogen (5 mg conjugated estrogens per day), comparable to those used to treat cancer of the prostate and breast, have been shown in a large prospective clinical trial in men to increase the risks of nonfatal myocardial infarction, pulmonary embolism, and thrombophlebitis.

b. Venous thromboembolism (VTE)

In the Women's Health Initiative (WHI) study, in women receiving CE compared to placebo, the risk of VTE (including both DVT and PE) was increased 33% (28 vs. 21 per 10,000 person-years) although only the increased rate of DVT reached statistical significance (p = 0.03). (See CLINICAL PHARMACOLOGY, Clinical Studies.)

In the CE/MPA treatment substudy of WHI, a 2-fold greater rate of VTE, including deep venous thrombosis and pulmonary embolism, was observed in women receiving treatment with CE/MPA compared to women receiving placebo. The rate of VTE was 34 per 10,000 woman-years in the CE/MPA group compared to 16 per 10,000 woman-years in the placebo group. The increase in VTE risk was observed during the first year and persisted.

If feasible, estrogens should be discontinued at least 4 to 6 weeks before surgery of the type associated with an increased risk of thromboembolism, or during periods of prolonged immobilization.

2. Malignant neoplasms

a. Endometrial cancer

The use of unopposed estrogens in women with intact uteri has been associated with an increased risk of endometrial cancer. The reported endometrial cancer risk among unopposed estrogen users was about 2-to-12-fold greater than in non-users, and appears dependent on duration of treatment and on estrogen dose. Most studies show no significant increased risk associated with use of estrogens for less than one year. The greatest risk appears associated with prolonged use, with increased risks of 15-to-24-fold for five to ten years or more and this risk has been shown to persist for at least 8 to 15 years after estrogen therapy is discontinued.

Clinical surveillance of all women taking estrogen/progestin combinations is important. Adequate diagnostic measures, including endometrial sampling when indicated, should be undertaken to rule out malignancy in all cases of undiagnosed persistent or recurring abnormal vaginal bleeding. There is no evidence that the use of natural estrogens results in a different endometrial risk profile than synthetic estrogens of equivalent estrogen dose. Adding a progestin to estrogen therapy has been shown to reduce the risk of endometrial hyperplasia, which may be a precursor to endometrial cancer.

b. Breast cancer

The most important randomized clinical trial providing information about breast cancer in estrogen plus progestin users is the WHI substudy of daily CE (0.625 mg) plus MPA (2.5 mg). After a mean follow-up of 5.6 years the estrogen plus progestin substudy reported an increased risk of invasive breast cancer in women who took daily CE plus MPA. In this substudy, prior use of estrogen-alone or estrogen plus progestin therapy was reported by 26 percent of the women. The relative risk of invasive breast cancer was 1.24, and the absolute risk was 41 versus 33 cases per 10,000 women-years, for CE plus MPA compared with placebo. Among women who reported prior use of hormone therapy, the relative risk of invasive breast cancer was 1.86, and the absolute risk was 46 versus 25 cases per 10,000 women-years, for CE plus MPA compared with placebo. Among women who reported no prior use of hormone therapy, the relative risk of invasive breast cancer was 1.09, and the absolute risk was 40 versus 36 cases per 10,000 women-years, for CE plus MPA compared with placebo. In the same substudy, invasive breast cancers were larger, were more likely to be node positive, and were diagnosed at a more advanced stage in the CE (0.625 mg) plus MPA (2.5 mg) group compared with the placebo group. Metastatic disease was rare with no apparent difference between the two groups. Other prognostic factors such as histologic subtype, grade and hormone receptor status did not differ between groups.

The most important randomized clinical trial providing information about breast cancer in estrogen-alone users is the WHI substudy of daily CE (0.625 mg)-alone. In the WHI estrogen-alone substudy, after an average follow-up of 7.1 years, daily CE (0.625 mg) alone was not associated with an increased risk of invasive breast cancer [relative risk (RR) 0.80].

Consistent with the Women’s Health Initiative (WHI clinical trials), observational studies have also reported an increased risk of breast cancer for estrogen plus progestin therapy and a smaller, but still increased risk, for estrogen-alone therapy after several years of use. One large meta-analysis of prospective cohort studies reported increased risks that were dependent upon duration of use and could last up to >10 years after discontinuation of estrogen plus progestin therapy and estrogen-alone therapy. Extension of the WHI trials also demonstrated increased breast cancer risk associated with estrogen plus progestin therapy. Observational studies also suggest that the risk of breast cancer was greater, and became apparent earlier, with estrogen plus progestin therapy as compared to the risk with estrogen-alone therapy. However, these studies have not found significant variation in the risk of breast cancer among different estrogen plus progestin combinations, doses, or routes of administration.

The use of estrogen-alone and estrogen plus progestin has been reported to result in an increase in abnormal mammograms requiring further evaluation. All women should receive yearly breast examinations by a healthcare provider and perform monthly breast self-examinations.

In addition, mammography examinations should be scheduled based on patient age, risk factors, and prior mammogram results.

3. Dementia

In the Women's Health Initiative Memory Study (WHIMS), 4,532 generally healthy postmenopausal women 65 years of age and older were studied, of whom 35% were 70 to 74 years of age and 18% were 75 or older. After an average follow-up of 4 years, 40 women being treated with CE/MPA (1.8%, n= 2,229) and 21 women in the placebo group (0.9%, n= 2,303) received diagnoses of probable dementia. The relative risk for CE/MPA versus placebo was 2.05 (95% confidence interval 1.21 – 3.48), and was similar for women with and without histories of menopausal hormone use before WHIMS. The absolute risk of probable dementia for CE/MPA versus placebo was 45 versus 22 cases per 10,000 women-years. It is unknown whether these findings apply to younger postmenopausal women. (See CLINICAL PHARMACOLOGY, Clinical Studies and PRECAUTIONS, Geriatric Use.)

4. Gallbladder disease

A 2- to 4-fold increase in the risk of gallbladder disease requiring surgery in postmenopausal women receiving estrogen has been reported.

5. Hypercalcemia

Estrogen administration may lead to severe hypercalcemia in patients with breast cancer and bone metastases. If hypercalcemia occurs, use of the drug should be stopped and appropriate measures taken to reduce the serum calcium level.

6. Visual abnormalities

Retinal vascular thrombosis has been reported in patients receiving estrogens. Discontinue medication pending examination if there is sudden partial or complete loss of vision, or a sudden onset of proptosis, diplopia, or migraine. If examination reveals papilledema or retinal vascular lesions, estrogens should be permanently discontinued.

7. Hereditary angioedema

In women with hereditary angioedema, exogenous estrogens may induce or exacerbate symptoms of angioedema.

PRECAUTIONS

A. General

1. Addition of progestin when a woman has not had a hysterectomy

Studies of the addition of a progestin for 10 or more days of a cycle of estrogen administration, or daily with estrogen in a continuous regimen, have reported a lowered incidence of endometrial hyperplasia than would be induced by estrogen treatment alone. Endometrial hyperplasia may be a precursor to endometrial cancer.

There are, however, possible risks that may be associated with the use of progestins with estrogens compared to estrogen-alone regimens. These include a possible increased risk of breast cancer, adverse effects on lipoprotein metabolism (e.g., lowering HDL, raising LDL) and impairment of glucose tolerance.

2. Elevated blood pressure

In a small number of case reports, substantial increases in blood pressure have been attributed to idiosyncratic reactions to estrogens. In a large, randomized, placebo-controlled clinical trial, a generalized effect of estrogens on blood pressure was not seen. Blood pressure should be monitored at regular intervals with estrogen use.

3. Hypertriglyceridemia

In patients with pre-existing hypertriglyceridemia, estrogen therapy may be associated with elevations of plasma triglycerides leading to pancreatitis and other complications.

4. Impaired liver function and past history of cholestatic jaundice

Estrogens may be poorly metabolized in patients with impaired liver function. For patients with a history of cholestatic jaundice associated with past estrogen use or with pregnancy, caution should be exercised and in the case of recurrence, medication should be discontinued.

5. Hypothyroidism

Estrogen administration leads to increased thyroid-binding globulin (TBG) levels. Patients with normal thyroid function can compensate for the increased TBG by making more thyroid hormone, thus maintaining free T4 and T3 serum concentrations in the normal range. Patients dependent on thyroid hormone replacement therapy who are also receiving estrogens may require increased doses of their thyroid replacement therapy. These patients should have their thyroid function monitored in order to maintain their free thyroid hormone levels in an acceptable range.

6. Fluid retention

Because estrogens may cause some degree of fluid retention, patients with conditions that might be influenced by this factor, such as a cardiac or renal dysfunction, require careful observation when estrogens are prescribed.

7. Hypocalcemia

Estrogens should be used with caution in individuals with severe hypocalcemia.

8. Ovarian cancer

The CE/MPA substudy of WHI reported that estrogen plus progestin increased the risk of ovarian cancer. After an average follow-up of 5.6 years, the relative risk for ovarian cancer for CE/MPA versus placebo was 1.58 (95% confidence interval 0.77 – 3.24) but was not statistically significant. The absolute risk for CE/MPA versus placebo was 20 versus 12 cases per 10,000 women-years. In some epidemiologic studies, the use of estrogen alone, in particular for ten or more years, has been associated with an increased risk of ovarian cancer. Other epidemiologic studies have not found these associations.

9. Exacerbation of endometriosis

Endometriosis may be exacerbated with administration of estrogens. A few cases of malignant transformation of residual endometrial implants have been reported in women treated post-hysterectomy with estrogen-alone therapy. For patients known to have residual endometriosis post-hysterectomy, the addition of progestin should be considered.

10. Exacerbation of other conditions

Estrogens may cause an exacerbation of asthma, diabetes mellitus, epilepsy, migraine or porphyria, systemic lupus erythematosus, and hepatic hemangiomas and should be used with caution in women with these conditions.

B. PATIENT INFORMATION

Physicians are advised to discuss the PATIENT INFORMATION leaflet with patients for whom they prescribe DEPO-Estradiol.

C. LABORATORY TESTS

Estrogen administration should be initiated at the lowest dose for the approved indication and then guided by clinical response, rather than by serum hormone levels (e.g., estradiol, FSH).

D. DRUG/LABORATORY TEST INTERACTIONS

1. Accelerated prothrombin time, partial thromboplastin time, and platelet aggregation time; increased platelet count; increased factors II, VII antigen, VIII antigen, VIII coagulant activity, IX, X, XII, VII-X complex, II-VII-X complex, and beta-thromboglobulin; decreased levels of anti-factor Xa and antithrombin III, decreased antithrombin III activity; increased levels of fibrinogen and fibrinogen activity; increased plasminogen antigen and activity.
2. Increased thyroid-binding globulin (TBG) levels leading to increased circulating total thyroid hormone, as measured by protein-bound iodine (PBI), T4 levels (by column or by radioimmunoassay) or T3 levels by radioimmunoassay. T3 resin uptake is decreased, reflecting the elevated TBG. Free T4 and free T3 concentrations are unaltered. Patients on thyroid replacement therapy may require higher doses of thyroid hormone.
3. Other binding proteins may be elevated in serum, i.e., corticosteroid binding globulin (CBG), sex-hormone binding globulin (SHBG), leading to increased circulating corticosteroids and sex steroids, respectively. Free or biologically active hormone levels concentrations are unchanged. Other plasma proteins may be increased (angiotensinogen/renin substrate, alpha-1-anti-trypsin, ceruloplasmin).
4. Increased plasma HDL and HDL-2 subfraction concentrations, reduced LDL cholesterol concentration, increased triglycerides levels.
5. Impaired glucose tolerance.
6. Reduced response to metyrapone test.
7. Reduced serum folate concentration.

E. CARCINOGENESIS, MUTAGENESIS, IMPAIRMENT OF FERTILITY

Long-term continuous administration of natural and synthetic estrogens in certain animal species increases the frequency of carcinomas of the breast, uterus, cervix, vagina, testis, and liver. (See BOXED WARINGS, WARNINGS and PRECAUTIONS.)

F. PREGNANCY

DEPO-Estradiol should not be used during pregnancy. See CONTRAINDICATIONS and Boxed WARNINGS.

G. NURSING MOTHERS

Estrogen administration to nursing mothers has been shown to decrease the quantity and quality of the milk. Detectable amounts of estrogens have been identified in the milk of mothers receiving this drug. Caution should be exercised when DEPO-Estradiol is administered to a nursing woman.

H. GERIATRIC USE

In the Women's Health Initiative Memory Study, including 4,532 women 65 years of age and older, followed for an average of 4 years, 82% (n= 3,729) were 65 to 74 while 18% (n= 803) were 75 and over. Most women (80%) had no prior hormone therapy use. Women treated with conjugated estrogens plus medroxyprogesterone acetate were reported to have a two-fold increase in the risk of developing probable dementia. Alzheimer's disease was the most common classification of probable dementia in both the conjugated estrogens plus medroxyprogesterone acetate group and the placebo group. Ninety percent of the cases of probable dementia occurred in the 54% of women that were older than 70. (See WARNINGS, Dementia.)

ADVERSE REACTIONS

See BOXED WARNINGS, WARNINGS and PRECAUTIONS.

The following additional adverse reactions have been reported with estrogens and/or progestin therapy.

1. Genitourinary system
  Changes in vaginal bleeding pattern and abnormal withdrawal bleeding or flow; breakthrough bleeding, spotting; dysmenorrhea; increase in size of uterine leiomyomata; vaginitis including vaginal candidiasis; change in amount of cervical secretion; changes in cervical ectropion; ovarian cancer; endometrial hyperplasia; endometrial cancer.
2. Breasts
  Tenderness, enlargement pain, nipple discharge, galactorrhea; fibrocystic breast changes; breast cancer.
3. Cardiovascular
  Deep and superficial venous thrombosis; pulmonary embolism; thrombophlebitis; myocardial infarction; stroke; increase in blood pressure.
4. Gastrointestinal
  Nausea, vomiting; abdominal cramps, bloating; cholestatic jaundice; increased incidence of gallbladder disease; pancreatitis, enlargement of hepatic hemangiomas.
5. Skin
  Chloasma or melasma that may persist when drug is discontinued. Erythema multiforme; erythema nodosum; hemorrhagic eruption; loss of scalp hair; hirsutism; pruritus, rash.
6. Eyes
  Retinal vascular thrombosis; steepening of corneal curvature; intolerance to contact lenses.
7. Central nervous system
  Headache, migraine, dizziness; mental depression; chorea; nervousness; mood disturbances; irritability; exacerbation of epilepsy, dementia.
8. Miscellaneous
  Increase or decrease in weight; reduced carbohydrate tolerance; aggravation of porphyria; edema; changes in libido; arthralgias; leg cramps; anaphylactoid/anaphylactic reactions including urticaria and angioedema; hypocalcemia; exacerbation of asthma; increased triglycerides.

DRUG ABUSE AND DEPENDENCE

Chlorobutanol anhydrous (chloral derivative) added as a preservative may be habit forming.

OVERDOSAGE

Serious ill effects have not been reported following acute ingestion of large doses of estrogen-containing oral contraceptives by young children. Overdosage of estrogen may cause nausea and vomiting, and withdrawal bleeding may occur in females.

DOSAGE AND ADMINISTRATION

Parenteral drug products should be inspected visually for particulate matter and discoloration prior to administration whenever solution and container permit.

Warming and shaking the vial should redissolve any crystals that may have formed during storage at temperatures lower than recommended.

DEPO-Estradiol INJECTION IS FOR INTRAMUSCULAR USE ONLY.

When estrogen is prescribed for a woman with a uterus, progestin should also be initiated to reduce the risk of endometrial cancer. A woman without a uterus does not need progestin. Use of estrogen, alone or in combination with a progestin, should be with the lowest effective dose and for the shortest duration consistent with treatment goals and risks for the individual woman. Patients should be reevaluated periodically as clinically appropriate (e.g., 3-month to 6-month intervals) to determine if treatment is still necessary. (See BOXED WARNINGS and WARNINGS.) For women who have a uterus, adequate diagnostic measures, such as endometrial sampling, when indicated, should be undertaken to rule out malignancy in cases of undiagnosed persistent or recurring abnormal vaginal bleeding.

1. Short-term cyclic use for treatment of moderate to severe vasomotor symptoms, vulval and vaginal atrophy associated with the menopause, the lowest dose and regimen that will control symptoms should be chosen and medication should be discontinued as promptly as possible.
  Attempts to discontinue or taper medication should be made at 3- to 6-month intervals. The usual dosage range is 1 to 5 mg injected every 3 to 4 weeks.
2. For treatment of female hypoestrogenism due to hypogonadism 1.5 to 2 mg injected at monthly intervals.

HOW SUPPLIED

DEPO-Estradiol Injection is available in the following concentration containing per mL:

5 mg estradiol cypionate; also 5.4 mg chlorobutanol anhydrous (chloral deriv.) added as preservative; in 913 mg cottonseed oil— in 5 mL vials, NDC 0009-0271-01.

WARNING: Chlorobutanol may be habit forming.

STORAGE AND HANDLING

Store at controlled room temperature 20° to 25° C (68° to 77° F) [see USP].

REFERENCES

1. Ziel HK, Finkle WD: Increased risk of endometrial carcinoma among users of conjugated estrogens. N Engl J Med 293:1167–1170, 1975.
2. Smith DC, Prentice R, Thompson DJ, et al: Association of exogenous estrogen and endometrial carcinoma. N Engl J Med 293:1164–1167, 1975.
3. Mack TM, Pike MC, Henderson BE, et al: Estrogens and endometrial cancer in a retirement community. N Engl J Med 294:1262–1267, 1976.
4. Weiss NS, Szekely DR, Austin DF: Increasing incidence of endometrial cancer in the United States. N Engl J Med 294:1259–1262, 1976.
5. Herbst AL, Ulfelder H, Poskanzer DC: Adenocarcinoma of the vagina. Association of maternal stilbestrol therapy with tumor appearance in young women. N Engl J Med 284:878–881, 1971.
6. Greenwald P, Barlow JJ, Nasca PC, Burnett WS: Vaginal cancer after maternal treatment with synthetic estrogens. N Engl J Med 285:390–392, 1971.
7. Lanier AP, Noller KL, Decker DG, Elveback LR, Kurland LT: Cancer and stilbestrol. A follow-up of 1,719 persons exposed to estrogens in utero and born 1943–1959. Mayo Clin Proc 48:793–799, 1973.
8. Herbst AL, Kurman RJ, Scully RE: Vaginal and cervical abnormalities after exposure to stilbestrol in utero. Obstet Gynecol 40:287–298, 1972.
9. Herbst AL, Robboy SJ, Macdonald GJ, Scully RE: The effects of local progesterone on stilbestrol-associated vaginal adenosis. Am J Obstet Gynecol 118:607–615, 1974.
10. Herbst AL, Poskanzer DC, Robboy SJ, Friedlander L, Scully RE: Prenatal exposure to stilbestrol. A prospective comparison of exposed female offspring with unexposed control. N Engl J Med 292:334–339, 1975.
11. Stafl A, Mattingly RF, Foley DV, Fetherston WC: Clinical diagnosis of vaginal adenosis. Obstet Gynecol 43:118–128, 1974.
12. Sherman AL, Goldrath M, Berlin A, et al: Cervical-vaginal adenosis after in utero exposure to synthetic estrogens. Obstet Gynecol 44:531545, 1974.
13. Gall, Kirman B, Stern J: Hormonal pregnancy tests and congenital malformation. Nature 216:83, 1967.
14. Levy EP, Cohen A, Fraser FC: Hormone treatment during pregnancy and congenital heart defects. Lancet 1:611, 1973.
15. Nora JJ, Nora AH: Birth defects and oral contraceptives. Lancet 1:941–942, 1973.
16. Janerich DT, Piper JM, Glebatis DM: Oral contraceptives and congenital limb-reduction defects. N Engl J Med 291:697–700, 1974.
17. Boston Collaborative Drug Surveillance Program: Surgically confirmed gall bladder disease, venous thromboembolism, and breast tumors in relation to post-menopausal estrogen therapy. N Engl J Med 290:15–19, 1974.
18. Hoover R, Gray LA, Cole P, MacMahon B: Menopausal estrogens and breast cancer. N Engl J Med 295:401–405, 1976.
19. Boston Collaborative Drug Surveillance Program: Oral contraceptives and venous thromboembolic disease, surgically confirmed gall bladder disease, and breast tumors. Lancet 1:1399–1404, 1973.
20. Daniel DG, Campbell H, Turnbull AC: Puerperal thromboembolism and suppression of lactation. Lancet 2:287–289, 1967.
21. The Veterans Administration Cooperative Urological Research Group: Carcinoma of the prostate: Treatment comparisons. J Urol 98:516522, 1967.
22. Bailar JC: Thromboembolism and estrogen therapy. Lancet 2:560, 1967.
23. Blackard CE, Doe RP, Mellinger GT, Byar DP: Incidence of cardiovascular disease and death in patients receiving diethylstilbestrol for carcinoma of the prostate. Cancer 26:249–256, 1970.
24. Royal College of General Practitioners: Oral contraception and thromboembolic disease. J R Coll Gen Pract 13:267–279, 1967.
25. Inman WHW, Vessey MP: Investigation of deaths from pulmonary, coronary, and cerebral thrombosis and embolism in women of childbearing age. Br Med J 2:193–199, 1968.
26. Vessey MP, Doll R: Investigation of relation between use of oral contraceptives and thromboembolic disease. A further report. Br Med J 2:651–657, 1969.
27. Sartwell PE, Masi AT, Arthes FG, et al: Thromboembolism and oral contraceptives: An epidemiologic case-control study. Am J Epidemiol 90:365–380, 1969.
28. Collaborative Group for the Study of Stroke in Young Women: Oral contraception and increased risk of cerebral ischemia or thrombosis. N Engl J Med 288:871–878, 1973.
29. Collaborative Group for the Study of Stroke in Young Women: Oral contraceptives and stroke in young women: Associated risk factors. JAMA 231:718–722, 1975.
30. Mann JI, Inman WHW: Oral contraceptives and death from myocardial infarction. Br Med J 2:245–248, 1975.
31. Mann JI, Vessey MP, Thorogood M, Doll R: Myocardial infarction in young women with special reference to oral contraceptive practice. Br Med J 2:241–245, 1975.
32. Inman WHW, Vessey MP, Westerholm B, Engelund A: Thromboembolic disease and the steroidal content of oral contraceptives. Br Med J 2:203–209, 1970.
33. Stolley PD, Tonascia JA, Tockman MS, et al: Thrombosis with low-estrogen oral contraceptives. Am J Epidemiol 102:197–208, 1975.
34. Vessey MP, Doll R, Fairbairn AS, Glober G: Postoperative thromboembolism and the use of oral contraceptives. Br Med J 3:123–126, 1970.
35. Greene GR, Sartwell PE: Oral contraceptive use in patients with thromboembolism following surgery, trauma or infection. Am J Public Health 62:680–685, 1972.
36. Rosenberg L, Armstrong B, Phil D, Jick H: Myocardial infarction and estrogen therapy in post-menopausal women. N Engl J Med 294:1256–1259, 1976.
37. Coronary Drug Project Research Group: The Coronary Drug Project: Initial findings leading to modifications of its research protocol. JAMA 214:1303–1313, 1970.
38. Baum J, Holtz F, Bookstein JJ, Klein EW: Possible association between benign hepatomas and oral contraceptives. Lancet 2:926–929, 1973.
39. Mays ET, Christopherson WM, Mahr MM, Williams HC: Hepatic changes in young women ingesting contraceptive steroids. Hepatic hemorrhage and primary hepatic tumors. JAMA 235:730–732, 1976.
40. Edmondson HA, Henderson B, Benton B: Liver-cell adenomas associated with use of oral contraceptives. N Engl J Med 294:470–472, 1976.
41. Pfeffer RI, VanDenNoort S: Estrogen use and stroke risk in post-menopausal women. Am J Epidemiol 103:445–456, 1976.

LAB-0083-6.0
Revised February 2024

PATIENT INFORMATION

DEPO-Estradiol®

Brand of estradiol cypionate injection, USP

Read this PATIENT INFORMATION before you start taking DEPO-Estradiol and read what you get each time you refill DEPO-Estradiol. There may be new information. This information does not take the place of talking to your healthcare provider about your medical condition or your treatment.

WHAT IS THE MOST IMPORTANT INFORMATION I SHOULD KNOW ABOUT DEPO-ESTRADIOL (AN ESTROGEN HORMONE)?

Estrogens increase the chances of getting cancer of the uterus.

Report any unusual vaginal bleeding right away while you are taking estrogens. Vaginal bleeding after menopause may be a warning sign of cancer of the uterine (womb). Your healthcare provider should check any unusual vaginal bleeding to find out the cause.

Do not use estrogens with or without progestins to prevent heart disease, heart attacks, or strokes.

Using estrogens with or without progestins may increase your chances of getting heart attacks, strokes, breast cancer, and blood clots. You and your healthcare provider should talk regularly about whether you still need treatment with DEPO-Estradiol.

What is DEPO-Estradiol?

Depo-Estradiol injection is an estrogen product. The information below is that which the U.S. Food and Drug Administration requires be provided for all patients taking estrogens. For further information ask your doctor.

What is DEPO-Estradiol used for?

DEPO-Estradiol is used during and after menopause to:

- reduce moderate or severe menopausal symptoms. Estrogens are hormones made by a woman's ovaries. The ovaries normally stop making estrogens when a woman is between 45 to 55 years old. This drop in body estrogen levels causes the "change of life" or menopause (end of monthly menstrual periods). Sometimes both ovaries are removed during an operation before natural menopause takes place, the sudden drop in estrogen levels causes "surgical menopause."
  When the estrogen levels begin dropping, some women develop very uncomfortable symptoms, such as feeling of warmth in the face, neck and chest or sudden strong feelings of heat and sweating ("hot flashes" or "hot flushes"). Using estrogen drugs can help the body adjust to lower estrogen levels and reduce these symptoms. Most women have only mild menopause symptoms or none at all and do not need estrogen drugs for these symptoms.
- treat moderate to severe itching, burning, and dryness in or around the vagina.
  You and your healthcare provider should talk regularly about whether you still need treatment with DEPO-Estradiol to control these problems.

DEPO-Estradiol is also used to:

- treat certain conditions in women before menopause if their ovaries do not make enough estrogen.

Who should not take DEPO-Estradiol?

Do not start taking DEPO-Estradiol if you:

- have unusual vaginal bleeding.
- currently have or have had certain cancers.
  Estrogens may increase the chances of getting certain types of cancers, including cancer of the breast or uterus. If you have or had cancer, talk with your healthcare provider about whether you should take DEPO-Estradiol.
- had a stroke or heart attack in the past year.
- currently have or have had blood clots.
- are allergic to DEPO-Estradiol or any of its ingredients.

See the end of this leaflet for a list of ingredients in DEPO-Estradiol.

- think you may be pregnant.

Tell your healthcare provider:

- if you are breastfeeding.

The hormone in DEPO-Estradiol can pass into your milk.

- about all of your medical problems.
  Your healthcare provider may need to check you more carefully if you have certain medical conditions, such as asthma (wheezing), epilepsy (seizures), diabetes, migraine, endometriosis, lupus, angioedema (swelling of face and tongue), hypertension (high blood pressure), problems with your heart, liver, thyroid, kidneys, or have high calcium levels in your blood.
- about all the medicines you take.
  This includes prescription and nonprescription medicines, vitamins, and herbal supplements. Some medicines may affect how DEPO-ESTRADIOL works. DEPO-ESTRADIOL may also affect how your other medicines work.
- if you are going to have surgery or will be on bed rest.
  You may need to stop taking estrogens.

How should I take DEPO-Estradiol?

Take DEPO-Estradiol as directed by your healthcare provider.

Estrogens should be used only as long as needed. You and your healthcare provider should talk regularly (for example, every 3 to 6 months) about whether you still need treatment with DEPO-ESTRADIOL.

What are the possible side effects of estrogens?

Less common but serious side effects include:

- Breast cancer
- Cancer of the uterus
- Stroke
- Heart attack
- Blood clots
- Gallbladder disease
- Ovarian cancer

These are some of the warning signs of serious side effects:

- Breast lumps
- Unusual vaginal bleeding
- Dizziness and faintness
- Changes in speech
- Severe headaches
- Chest pain
- Shortness of breath
- Pains in your legs
- Changes in vision
- Vomiting

Call your healthcare provider right away if you get any of these warning signs, or any other unusual symptom that concerns you.

Common side effects include:

- Headache
- Breast pain
- Irregular vaginal bleeding or spotting
- Stomach/abdominal cramps, bloating
- Nausea and vomiting

Other side effects include:

- High blood pressure
- Liver problems
- High blood sugar
- Fluid retention
- Enlargement of benign tumors of the uterus ("fibroids")
- Vaginal yeast infections
- Hair loss

These are not all the possible side effects of DEPO-Estradiol. For more information, ask your healthcare provider or pharmacist.

What can I do to lower my chances of getting a serious side effect with DEPO-Estradiol?

- Talk with your healthcare provider regularly about whether you should continue taking DEPO-ESTRADIOL. If you have a uterus, talk to your healthcare provider about whether the addition of a progestin is right for you. See your healthcare provider right away if you get vaginal bleeding while taking DEPO-ESTRADIOL. Have a breast exam and mammogram (breast X-ray) every year unless your healthcare provider tells you something else. If members of your family have had breast cancer or if you have ever had breast lumps or an abnormal mammogram, you may need to have breast examinations more often. If you have high blood pressure, high cholesterol (fat in the blood), diabetes, are overweight, or if you use tobacco, you may have higher chances for getting heart disease. Ask your healthcare provider for ways to lower your chances for getting heart disease.

General information about safe and effective use of DEPO-Estradiol

Medicines are sometimes prescribed for conditions that are not mentioned in patient information leaflets. Do not take DEPO-Estradiol for conditions for which it was not prescribed. Do not give DEPO-Estradiol to other people, even if they have the same symptoms you have. It may harm them. Keep DEPO-Estradiol out of the reach of children.

This leaflet provides a summary of the most important information about DEPO-Estradiol. If you would like more information, talk with your healthcare provider or pharmacist. You can ask for information about DEPO-Estradiol that is written for health professionals. You can get more information by calling the toll free number 1-800-438-1985. You are cautioned to discuss very carefully with your doctor or healthcare provider all the possible risks and benefits of long-term estrogen and progestin treatment as they affect you personally.

Rx only

LAB-0900-2.0
Revised June 2019

PRINCIPAL DISPLAY PANEL - 5 mg/mL Vial Label

5 mL Vial
NDC 0009-0271-01

Depo®-Estradiol
estradiol cypionate injection, USP

5 mg/mL

For intramuscular use only

Rx only

PRINCIPAL DISPLAY PANEL - 5 mg/mL Vial Carton

NDC 0009-0271-01
Rx only

1–5 mL Vial

Depo®-Estradiol
estradiol cypionate
injection, USP

5 mg/mL

For intramuscular use only

Pfizer Injectables